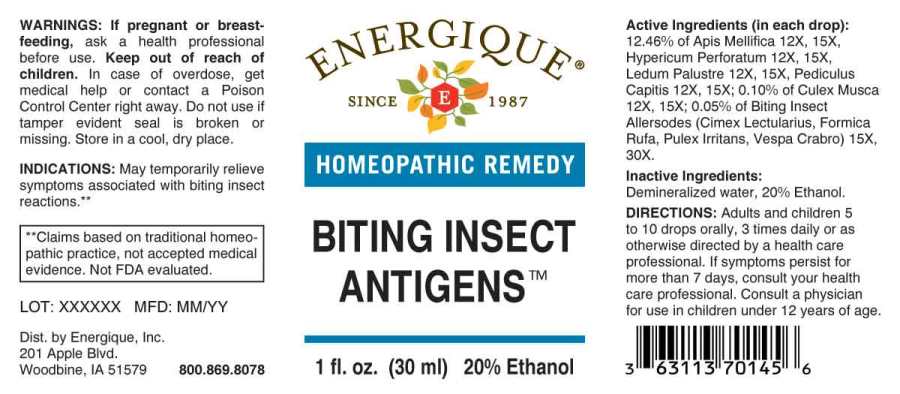 DRUG LABEL: Biting Insect Antigens
NDC: 44911-0648 | Form: LIQUID
Manufacturer: Energique, Inc.
Category: homeopathic | Type: HUMAN OTC DRUG LABEL
Date: 20231117

ACTIVE INGREDIENTS: APIS MELLIFERA 12 [hp_X]/1 mL; CULEX PIPIENS 12 [hp_X]/1 mL; HYPERICUM PERFORATUM WHOLE 12 [hp_X]/1 mL; RHODODENDRON TOMENTOSUM LEAFY TWIG 12 [hp_X]/1 mL; PEDICULUS HUMANUS VAR. CAPITIS 12 [hp_X]/1 mL; CIMEX LECTULARIUS 15 [hp_X]/1 mL; FORMICA RUFA 15 [hp_X]/1 mL; PULEX IRRITANS WHOLE 15 [hp_X]/1 mL; VESPA CRABRO 15 [hp_X]/1 mL
INACTIVE INGREDIENTS: WATER; ALCOHOL

Drug Facts:

ACTIVE INGREDIENTS:

(in each drop): 12.46% of Apis Mellifica 12X, 15X, Hypericum Perforatum 12X, 15X, Ledum Palustre 12X, 15X; Pediculus Capitis 12X, 15X,0.10% of Culex Musca12X,15X; 0.05% of Biting Insect Allersodes (Cimex Lectularius, Formica Rufa, Pulex Irritans, Vespa Crabro) 15X, 30X.

INDICATIONS:

May temporarily relieve symptoms associated with biting insect reactions.**

**Claims based on traditional homeopathic practice, not accepted medical evidence. Not FDA evaluated.

WARNINGS:

If pregnant or breast-feeding, ask a health professional before use.

Keep out of reach of children. In case of overdose, get medical help or contact a Poison Control Center right away.

Do not use if tamper evident seal is broken or missing. Store in a cool, dry place.

KEEP OUT OF REACH OF CHILDREN:

In case of overdose, get medical help or contact a Poison Control Center right away.

DIRECTIONS:

Adults and children 5 to 10 drops orally, 3 times daily or as otherwise directed by a health care professional. If symptoms persist for more than 7 days, consult your health care professional. Consult a physician for use in children under 12 years of age.

INDICATIONS:

May temporarily relieve symptoms associated with biting insect reactions.**

**Claims based on traditional homeopathic practice, not accepted medical evidence. Not FDA evaluated.

INACTIVE INGREDIENTS:

Demineralized water, 20% Ethanol.

QUESTIONS:

Dist. by Energique, Inc.

201 Apple Blvd

Woodbine, IA 51579 800.869.8078

PACKAGE LABEL DISPLAY:

ENERGIQUE

SINCE 1987

HOMEOPATHIC REMEDY

BITING INSECT

ANTIGENS

1 fl. oz. (30 ml)